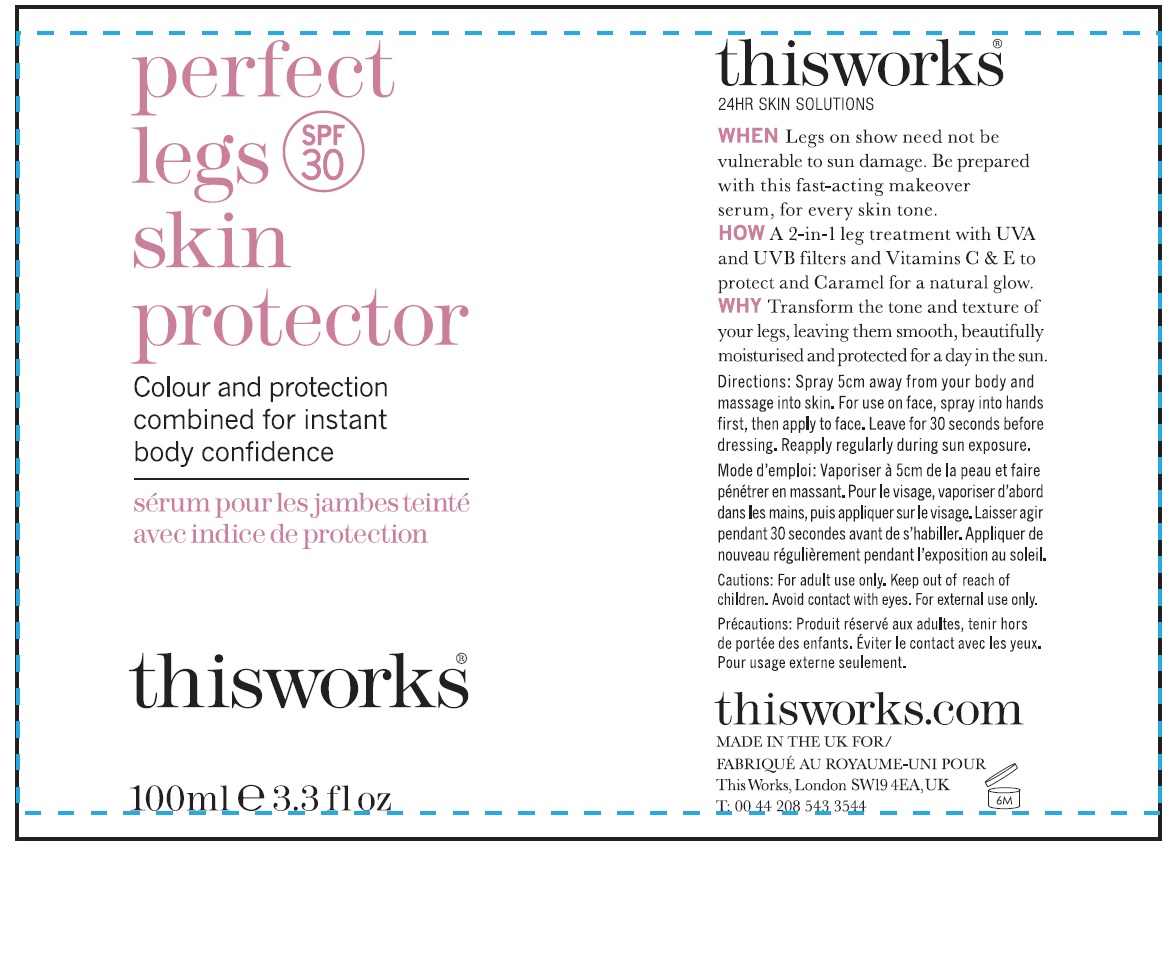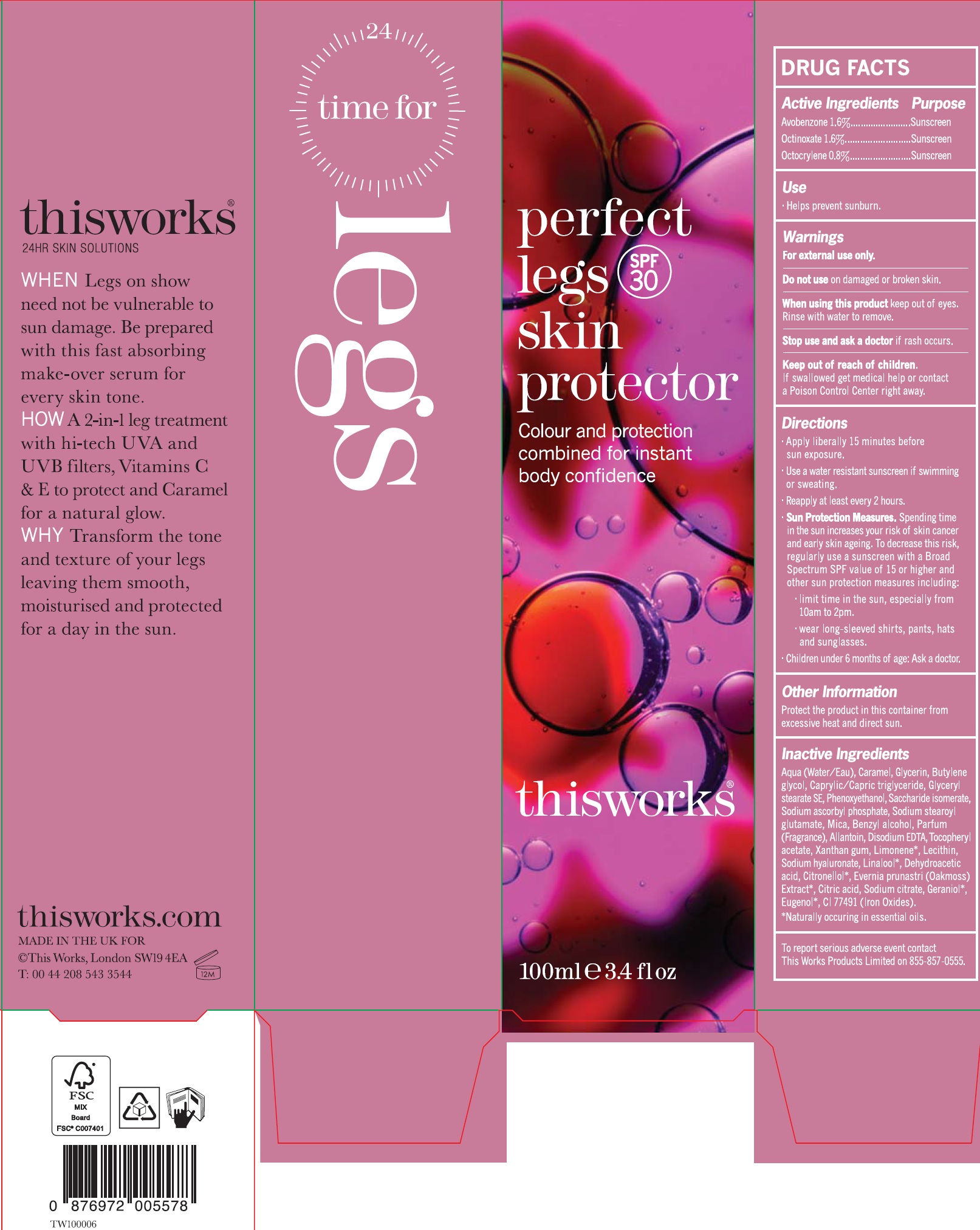 DRUG LABEL: Perfect Legs Skin Protector SPF 30
NDC: 71278-005 | Form: CREAM
Manufacturer: THIS WORKS PRODUCTS LIMITED
Category: otc | Type: HUMAN OTC DRUG LABEL
Date: 20231114

ACTIVE INGREDIENTS: AVOBENZONE 16 mg/1 mL; OCTINOXATE 16 mg/1 mL; OCTOCRYLENE 8 mg/1 mL
INACTIVE INGREDIENTS: WATER; CARAMEL; GLYCERIN; BUTYLENE GLYCOL; MEDIUM-CHAIN TRIGLYCERIDES; GLYCERYL STEARATE SE; PHENOXYETHANOL; SACCHARIDE ISOMERATE; SODIUM ASCORBYL PHOSPHATE; SODIUM STEAROYL GLUTAMATE; MICA; BENZYL ALCOHOL; ALLANTOIN; EDETATE DISODIUM ANHYDROUS; .ALPHA.-TOCOPHEROL ACETATE; XANTHAN GUM; LIMONENE, (+)-; HYALURONATE SODIUM; LINALOOL, (+/-)-; DEHYDROACETIC ACID; .BETA.-CITRONELLOL, (R)-; EVERNIA PRUNASTRI; CITRIC ACID MONOHYDRATE; SODIUM CITRATE; GERANIOL; EUGENOL; FERRIC OXIDE RED

Perfect Legs Skin Protector SPF 30

Active Ingredients

Avobenzone 1.6%

Octinoxate 1.6%

Octocrylene 0.8%

Purpose

Sunscreen

Use

- Helps prevent sunburn.

Warnings

For external use only.

Do not use

on damaged or broken skin.

When using this product

keep out of eyes. Rinse with water to remove.

Stop use and ask a doctor

if rash occurs.

Keep out of reach of children.

If swallowed get medical help or contact a Poison Control Center right away.

Directions

- Apply liberally 15 minutes before sun exposure.
- Use a water resistant sunscreen if swimming or sweating.
- Reapply at least every 2 hours.
- Spending time in the sun increases your risk of skin cancer and early skin ageing. To decrease this risk, regularly use a sunscreen with a Broad Spectrum SPF value of 15 or higher and other sun protection measures including: Sun Protection Measures.
- limit time in the sun, especially from 10am to2pm.
- wear long-sleeved shirts, pants, hats and sunglasses.
- Children under 6 months of age: Ask a doctor.

Other Information

Protect the product in this container from excessive heat and direct sun.

Inactive Ingredients

Aqua (Water/Eau), Caramel, Glycerin, Butylene glycol, Caprylic/Capric triglyceride, glyceryl stearate SE, Phenoxyethanol, Saccharide isomerate, Sodium ascorbyl phosphate, Sodium stearoyl glutamate, Mica, Benzyl alcohol, Parfum (Fragrance), Allantoin, Disodium EDTA, Tocopheryl acetate, Xanthan gum, Limonene, Lecithin, Sodium hyaluronate, Linalool, Dehydroacetic acid, Citronellol, Evernia prunastri (Oakmoss) Extract, Citric acid, Sodium citrate, Geraniol, Eugenol, CI 77491 (Iron Oxides).

*Naturally occuring in essential oils.